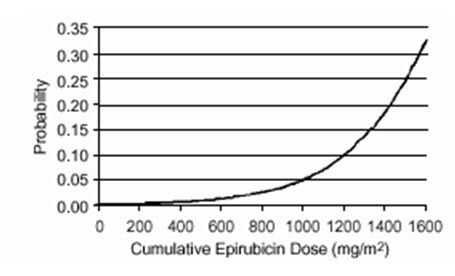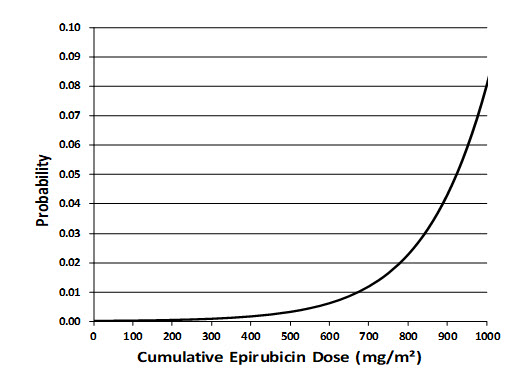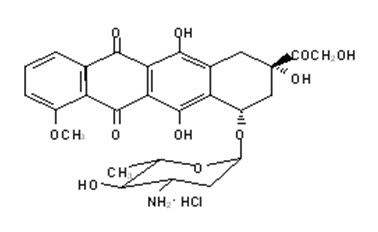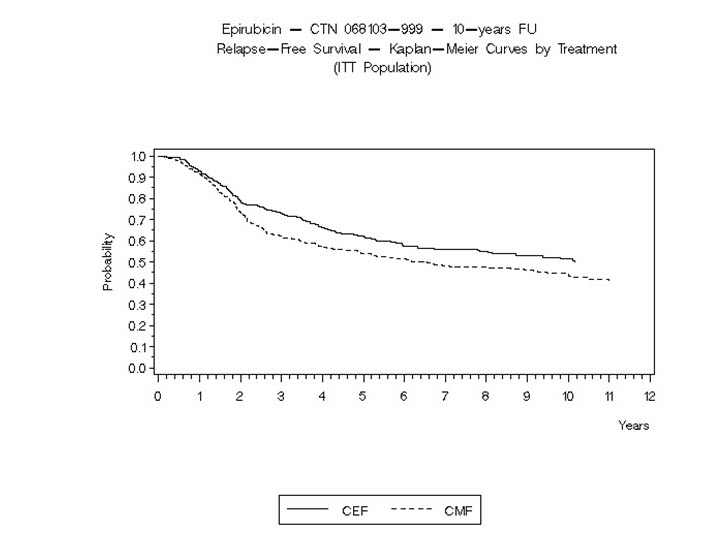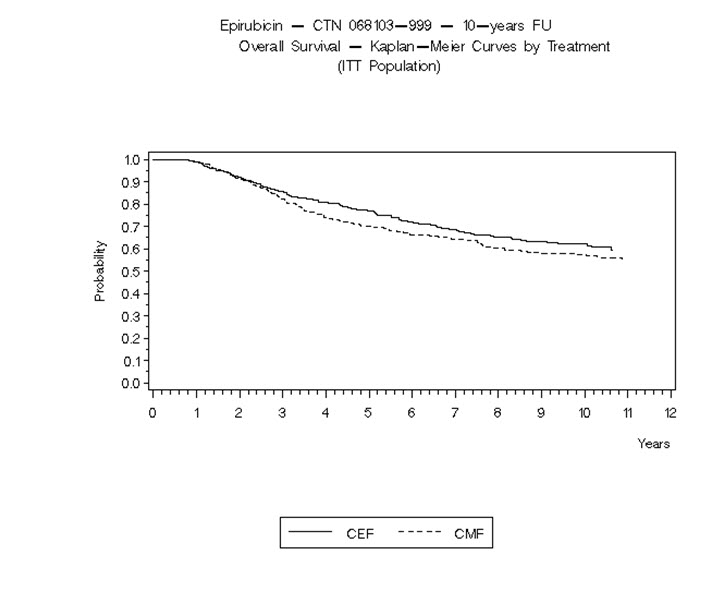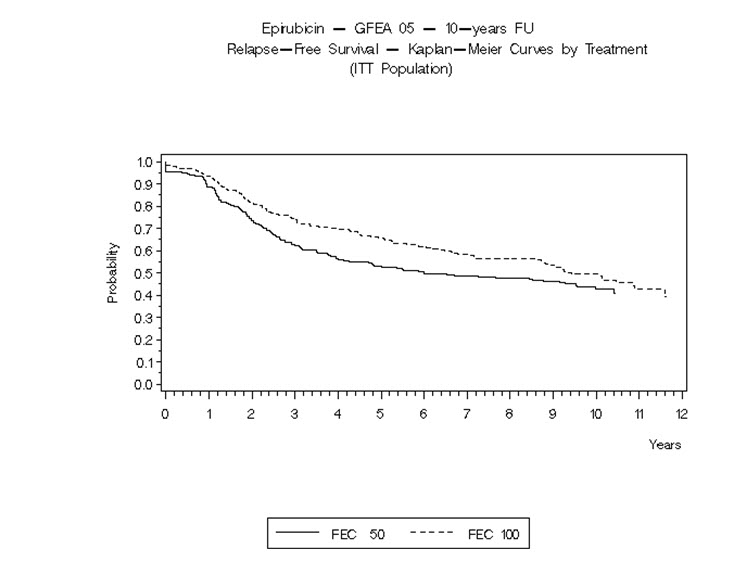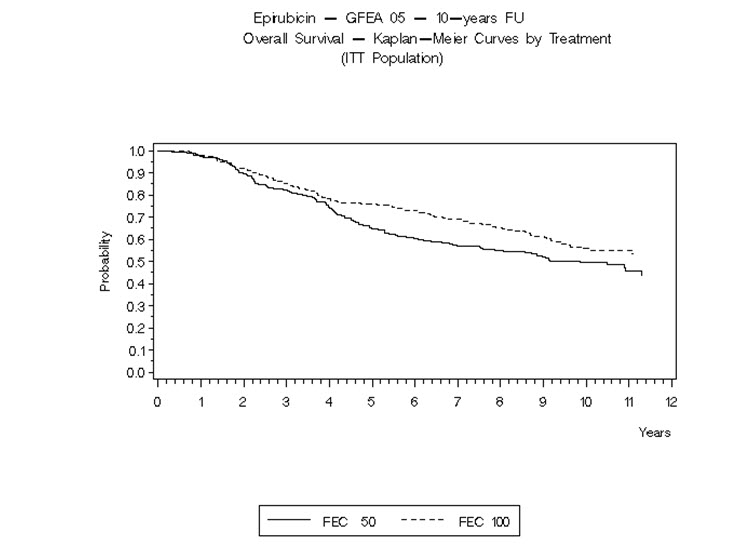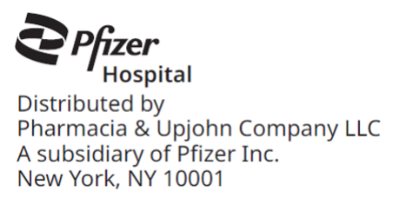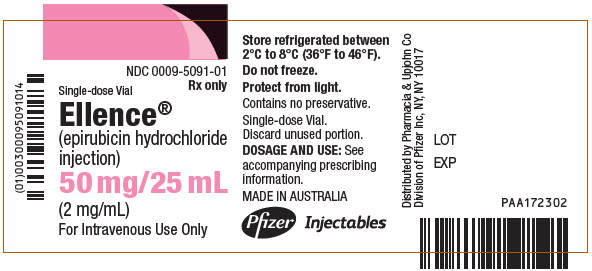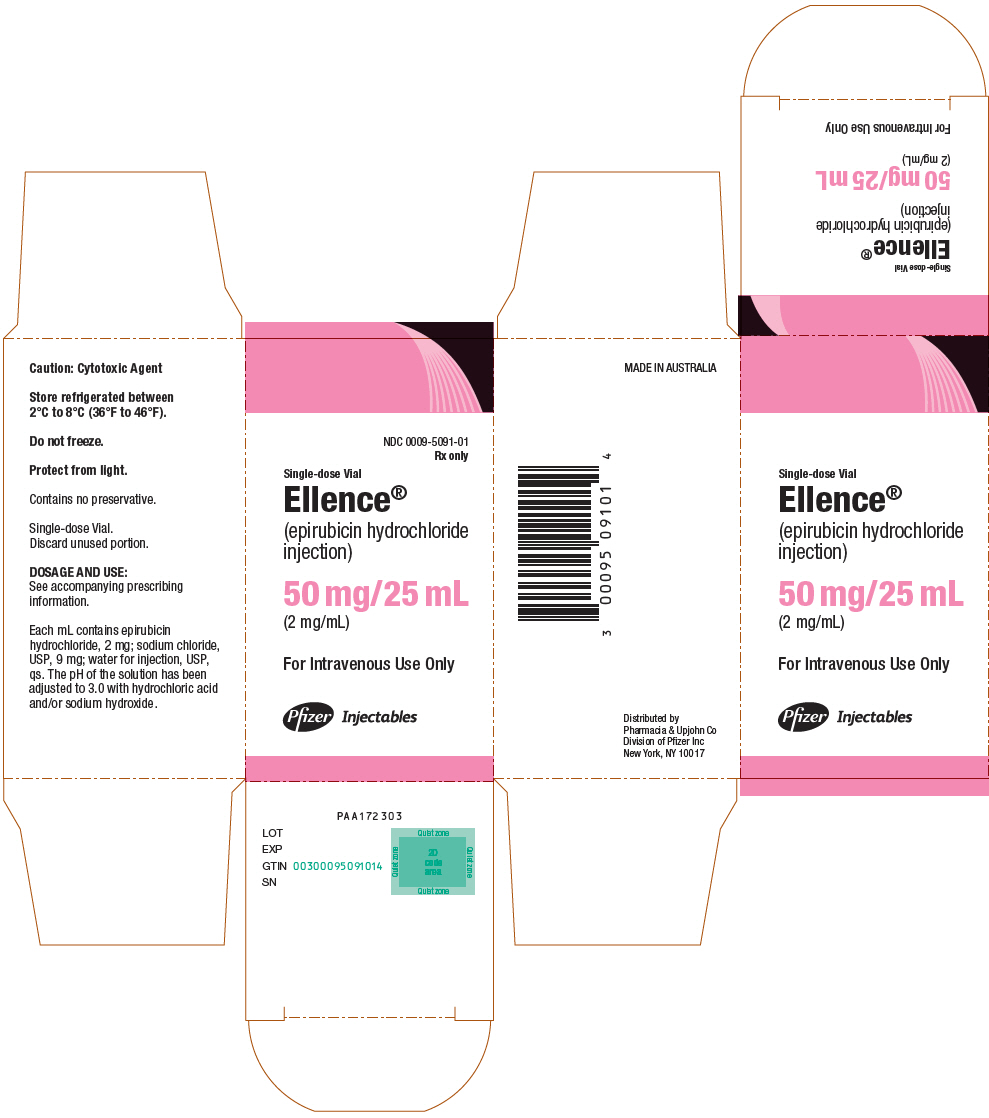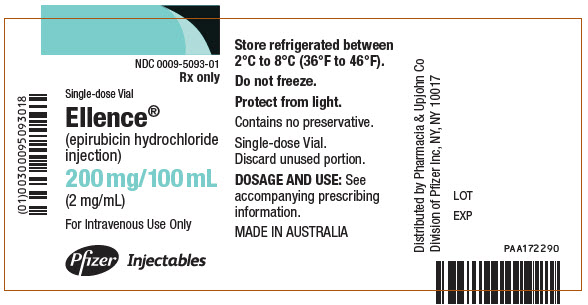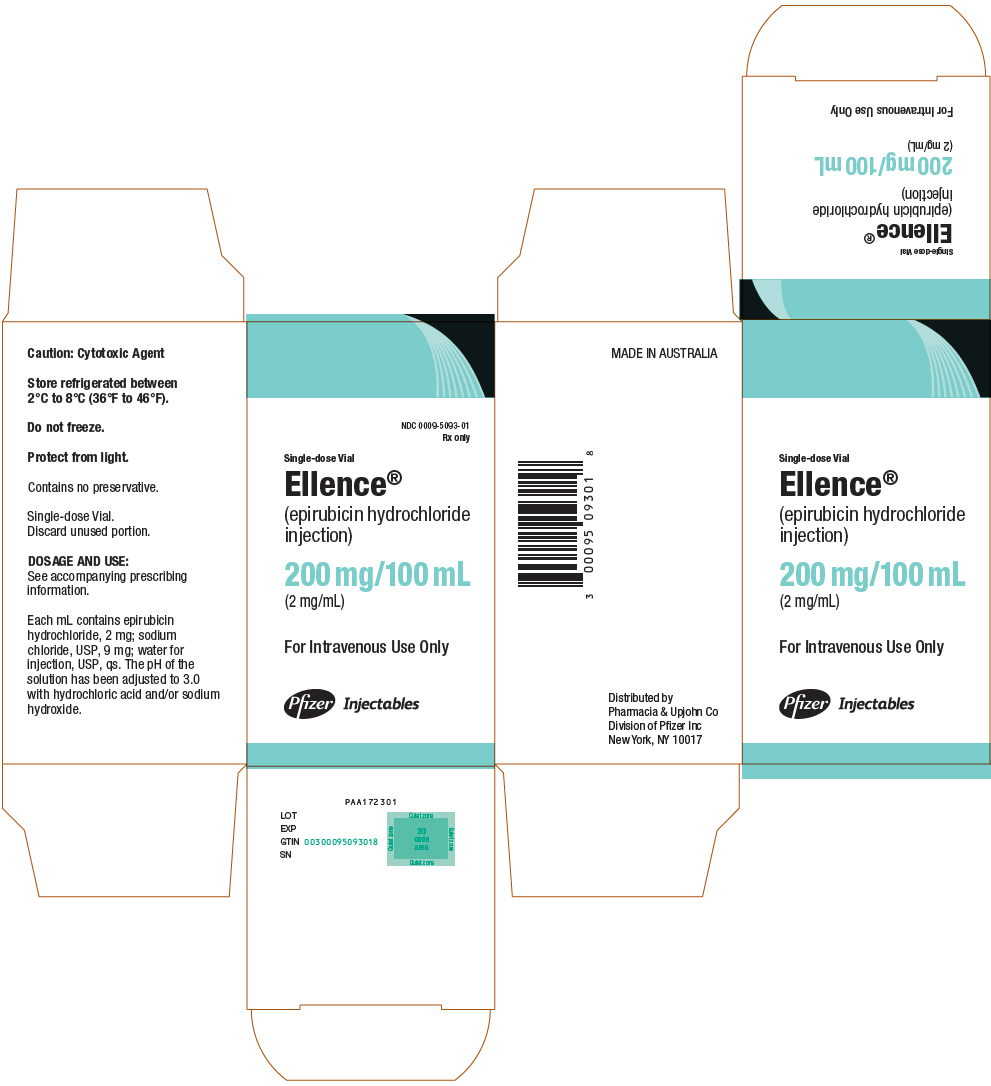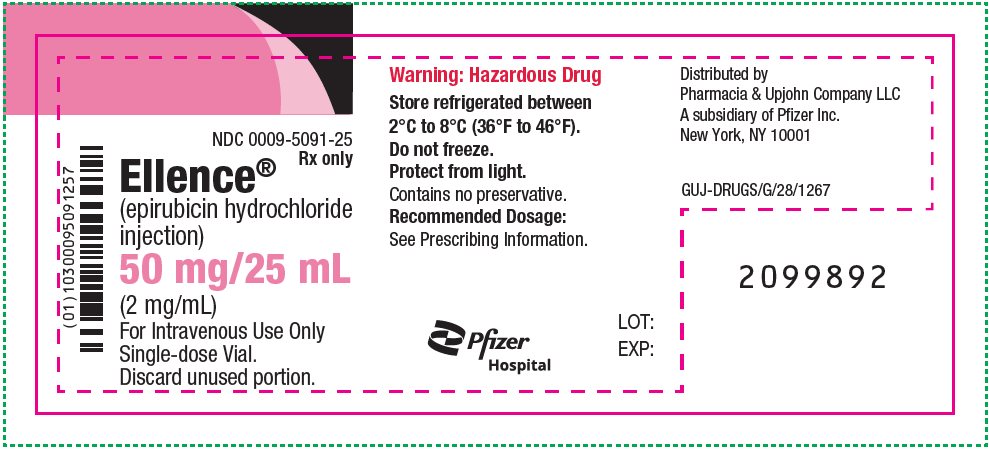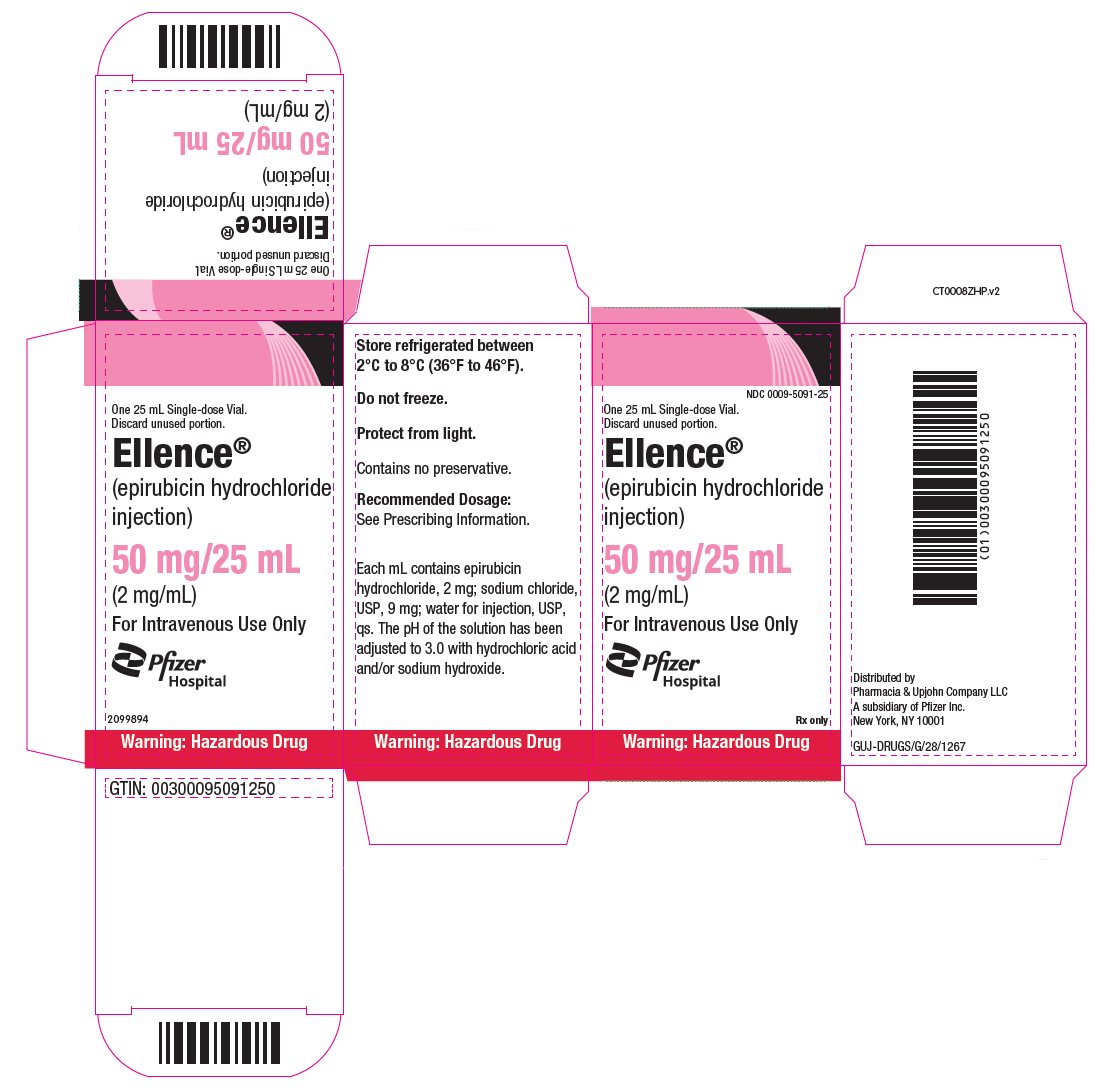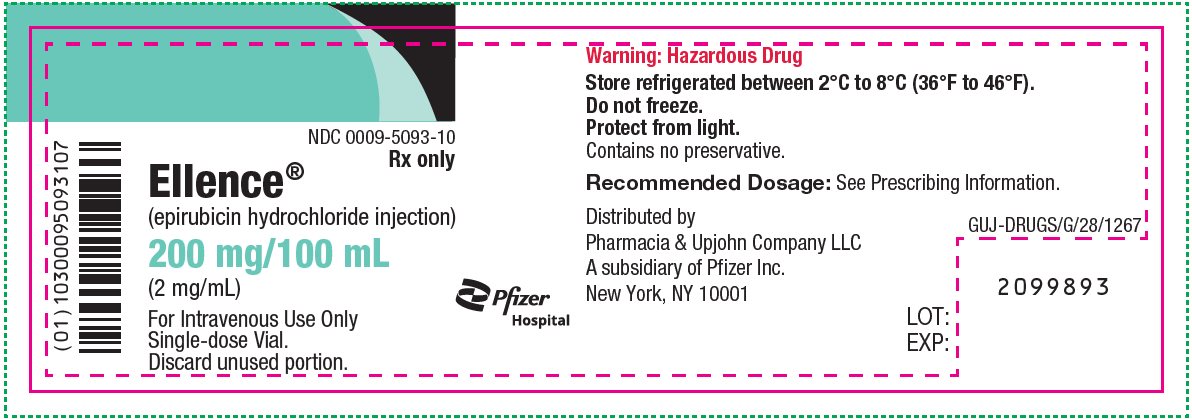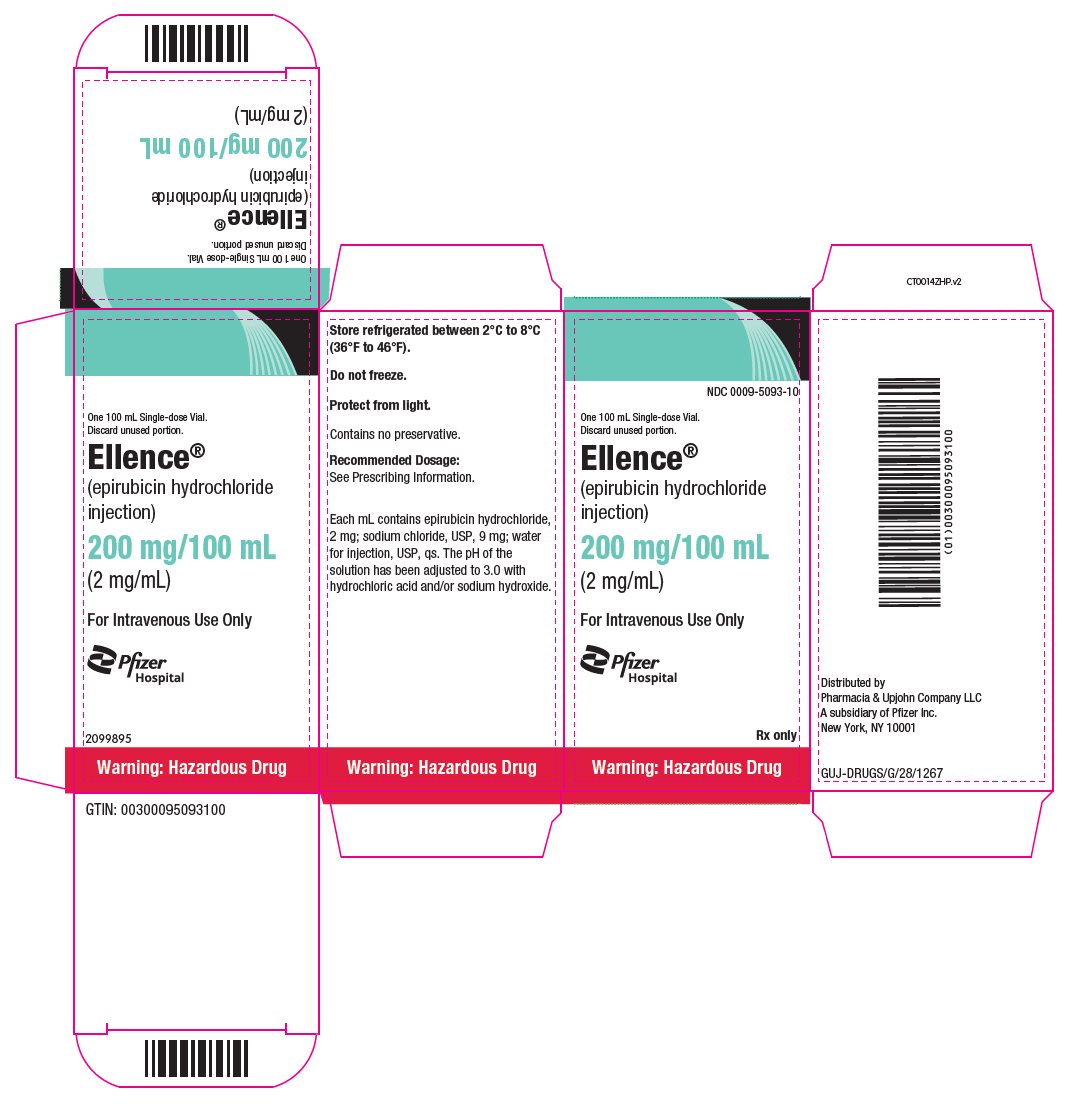 DRUG LABEL: Ellence
NDC: 0009-5091 | Form: INJECTION, SOLUTION
Manufacturer: Pharmacia & Upjohn Company LLC
Category: prescription | Type: HUMAN PRESCRIPTION DRUG LABEL
Date: 20250730

ACTIVE INGREDIENTS: EPIRUBICIN HYDROCHLORIDE 2 mg/1 mL
INACTIVE INGREDIENTS: SODIUM CHLORIDE; WATER; HYDROCHLORIC ACID; SODIUM HYDROXIDE

HIGHLIGHTS OF PRESCRIBING INFORMATION

These highlights do not include all the information needed to use ELLENCE safely and effectively. See full prescribing information for ELLENCE.
ELLENCE® (epirubicin hydrochloride injection)
Initial U.S. Approval: 1999

WARNING: CARDIAC TOXICITY, SECONDARY MALIGNANCIES, EXTRAVASATION AND TISSUE NECROSIS, and SEVERE MYELOSUPPRESSION

See full prescribing information for complete boxed warning.

- Cardiac Toxicity: Myocardial damage, including acute left ventricular failure, can occur with ELLENCE. The risk of cardiomyopathy is proportional to the cumulative exposure with incidence rates from 0.9% at a cumulative dose of 550 mg/m^2, 1.6% at 700 mg/m^2, and 3.3% at 900 mg/m^2. The risk of cardiomyopathy is further increased with concomitant cardiotoxic therapy. Assess left ventricular ejection fraction (LVEF) before and regularly during and after treatment with ELLENCE (5.1).
- Secondary Malignancies: Secondary acute myelogenous leukemia (AML) and myelodysplastic syndrome (MDS) occur at a higher incidence in patients treated with anthracyclines, including ELLENCE (5.2).
- Extravasation and Tissue Necrosis: Extravasation of ELLENCE can result in severe local tissue injury and necrosis requiring wide excision of the affected area and skin grafting. Immediately terminate the drug and apply ice to the affected area (5.3).
- Severe myelosuppression resulting in serious infection, septic shock, requirement for transfusions, hospitalization, and death may occur (5.4).

1 INDICATIONS AND USAGE

ELLENCE is an anthracycline topoisomerase inhibitor indicated as a component of adjuvant therapy in patients with evidence of axillary node tumor involvement following resection of primary breast cancer (1).

2 DOSAGE AND ADMINISTRATION

- The recommended starting dose of ELLENCE is 100 to 120 mg/m^2. Dosage reductions are possible when given in certain combinations (2.2).
- Administer intravenously in repeated 3- to 4-week cycles, either total dose on Day 1 of each cycle or divided equally and given on Days 1 and 8 of each cycle (2.2).
- Consider use of antiemetics when given in conjunction with other emetigenic drugs (2.1).
- Patients administered the 120 mg/m^2 regimen of ELLENCE should receive prophylactic antibiotic therapy (2.1).
- Adjust dosage after the first treatment cycle based on hematologic and nonhematologic toxicities (2.3).
- Reduce dose in patients with hepatic impairment (2.3, 8.6).
- Consider lower doses in patients with severe renal impairment (2.3, 8.7).

3 DOSAGE FORMS AND STRENGTHS

Injection: 50 mg/25 mL (2 mg/mL), 200 mg/100 mL (2 mg/mL) solution in single-dose vials (3).

4 CONTRAINDICATIONS

- Severe myocardial insufficiency (4).
- Recent myocardial infarction (4).
- Severe persistent drug-induced myelosuppression (4).
- Severe hepatic impairment (4).
- Severe hypersensitivity to ELLENCE, other anthracyclines, or anthracenediones (4).

5 WARNINGS AND PRECAUTIONS

- Use in Patients with Hepatic Impairment: Monitor serum total bilirubin and AST levels before and during treatment with ELLENCE. In patients with elevated serum AST or serum total bilirubin, dosage reductions or discontinuation may be required (2.3, 5.5).
- Tumor Lysis Syndrome: Evaluate blood uric acid levels, potassium, calcium, phosphate, and creatinine after initial treatment. Consider hydration, urine alkalinization, and prophylaxis with allopurinol to minimize potential complications of hyperuricemia and tumor lysis syndrome (5.7).
- Thrombophlebitis and Thromboembolic Events: Thrombophlebitis and thromboembolic events, including pulmonary embolism (in some cases fatal) have been reported with the use of ELLENCE. Venous sclerosis may result from an injection into a small vessel or from repeated injections into the same vein (5.9).
- Administration of live or live-attenuated vaccines in patients immunocompromised by chemotherapeutic agents including ELLENCE, may result in serious or fatal infections (5.7).
- Potentiation of Radiation Toxicity and Radiation Recall: Administration of ELLENCE after previous radiation therapy may induce an inflammatory recall reaction at the site of the irradiation (5.10).
- Embryo-Fetal Toxicity: ELLENCE can cause fetal harm. Advise patients of the potential risk to a fetus and to use effective contraception (5.11, 8.1, 8.3).

6 ADVERSE REACTIONS

The most common adverse reactions (≥10%) are leukopenia, neutropenia, anemia, thrombocytopenia, amenorrhea, lethargy, nausea/vomiting, mucositis, diarrhea, infection, conjunctivitis/keratitis, alopecia, local skin toxicity, and rash/itch (6).

To report SUSPECTED ADVERSE REACTIONS, contact Pfizer Inc at 1-800-438-1985 or FDA at 1-800-FDA-1088 or www.fda.gov/medwatch.

7 DRUG INTERACTIONS

- Avoid using cardiotoxic agents in combination with ELLENCE (7.1).
- Discontinue cimetidine during treatment with ELLENCE (7.2).

8 USE IN SPECIFIC POPULATIONS

- Lactation: Advise not to breastfeed (8.2).
- Females and Males of Reproductive Potential: May impair fertility (8.3).

FULL PRESCRIBING INFORMATION

WARNING: CARDIAC TOXICITY, SECONDARY MALIGNANCIES, EXTRAVASATION AND TISSUE NECROSIS, and SEVERE MYELOSUPPRESSION

- Cardiac Toxicity: Myocardial damage, including acute left ventricular failure, can occur with ELLENCE. The risk of cardiomyopathy is proportional to the cumulative exposure with incidence rates from 0.9% at a cumulative dose of 550 mg/m^2, 1.6% at 700 mg/m^2, and 3.3% at 900 mg/m^2. The risk of cardiomyopathy is further increased with concomitant cardiotoxic therapy. Assess left ventricular ejection fraction (LVEF) before and regularly during and after treatment with ELLENCE [see Warnings and Precautions (5.1)].
- Secondary Malignancies: Secondary acute myelogenous leukemia (AML) and myelodysplastic syndrome (MDS) occur at a higher incidence in patients treated with anthracyclines, including ELLENCE [see Warnings and Precautions (5.2)].
- Extravasation and Tissue Necrosis: Extravasation of ELLENCE can result in severe local tissue injury and necrosis requiring wide excision of the affected area and skin grafting. Immediately terminate the drug and apply ice to the affected area [see Warnings and Precautions (5.3)].
- Severe myelosuppression resulting in serious infection, septic shock, requirement for transfusions, hospitalization, and death may occur [see Warnings and Precautions (5.4)].

1 INDICATIONS AND USAGE

ELLENCE is indicated as a component of adjuvant therapy in patients with evidence of axillary node tumor involvement following resection of primary breast cancer [see Clinical Studies (14.1)].

2 DOSAGE AND ADMINISTRATION

2.1 Important Administration Instructions

When possible, to reduce the risk of developing cardiotoxicity in patients receiving ELLENCE after stopping treatment with other cardiotoxic agents, especially those with long half-lives such as trastuzumab, delay ELLENCE-based therapy until the other agents have cleared from the circulation [see Warnings and Precautions (5.1)].

Antiemetics may reduce nausea and vomiting; consider use of antiemetics before administration of ELLENCE or when clinically indicated, particularly when given in conjunction with other emetigenic drugs [see Adverse Reactions (6.1)].

Patients administered the 120 mg/m^2 regimen of ELLENCE should receive prophylactic antibiotic therapy.

2.2 Recommended Dose

The recommended dose of ELLENCE is 100 to 120 mg/m^2 administered as an intravenous bolus [see Dosage and Administration (2.4)].

The following regimens are recommended:

CEF-120: | Cyclophosphamide | 75 mg/m^2 oral on Days 1 to 14
 | ELLENCE | 60 mg/m^2 intravenously on Days 1 and 8
 | 5-Fluorouracil | 500 mg/m^2 intravenously on Days 1 and 8
 | Repeat every 28 days for 6 cycles
FEC-100: | 5-Fluorouracil | 500 mg/m^2 intravenously on Day 1
 | ELLENCE | 100 mg/m^2 intravenously on Day 1
 | Cyclophosphamide | 500 mg/m^2 intravenously on Day 1
 | Repeat every 21 days for 6 cycles

Administer ELLENCE in repeated 3- to 4-week cycles. The total dose of ELLENCE may be given on Day 1 of each cycle or divided equally and given on Days 1 and 8 of each cycle.

2.3 Dose Modifications

ELLENCE dosage adjustments for hematologic and non-hematologic toxicities within a cycle of treatment, is based on nadir platelet counts <50,000/mm^3, absolute neutrophil counts (ANC) <250/mm^3, neutropenic fever, or Grades 3/4 nonhematologic toxicity. Reduce ELLENCE Day 1 dose in subsequent cycles to 75% of the Day 1 dose given in the current cycle. Delay Day 1 chemotherapy in subsequent courses of treatment until platelet counts are ≥100,000/mm^3, ANC ≥1500/mm^3, and nonhematologic toxicities have recovered to ≤ Grade 1.

Cardiac Toxicity

Discontinue ELLENCE in patients who develop signs or symptoms of cardiomyopathy [see Warnings and Precautions (5.1)].

Bone Marrow Dysfunction

Consider administering a lower starting dose (75–90 mg/m^2) for heavily pretreated patients, patients with pre-existing bone marrow depression, or in the presence of neoplastic bone marrow infiltration [see Warnings and Precautions (5.4)]. For patients receiving a divided dose of ELLENCE (Day 1 and Day 8), the Day 8 dose should be 75% of Day 1 if platelet counts are 75,000–100,000/mm^3 and ANC is 1000 to 1499/mm^3. If Day 8 platelet counts are <75,000/mm^3, ANC <1000/mm^3, or Grades 3/4 nonhematologic toxicity has occurred, omit the Day 8 dose.

Hepatic Impairment

In patients with elevated serum AST or serum total bilirubin concentrations [see Warnings and Precautions (5.5) and Clinical Pharmacology (12.3)], reduce dosage as follows:

- Bilirubin 1.2 to 3 mg/dL or AST 2 to 4 times upper limit of normal 1/2 of recommended starting dose
- Bilirubin > 3 mg/dL or AST > 4 times upper limit of normal 1/4 of recommended starting dose

Renal Impairment

Consider lower doses in patients with severe renal impairment (serum creatinine > 5 mg/dL) [see Warnings and Precautions (5.6) and Clinical Pharmacology (12.3)].

2.4 Preparation and Administration Precautions

Preparation

Storage of the solution for injection at refrigerated conditions can result in the formation of a gelled product. This gelled product will return to a slightly viscous to mobile solution after 2 to a maximum of 4 hours equilibration at controlled room temperature (15–25°C).

Inspect parenteral drug products visually for particulate matter and discoloration prior to administration, whenever solution and container permit.

ELLENCE is a cytotoxic drug. Follow applicable special handling and disposable procedures^1 [see References (15)].

Incompatibilities

Avoid prolonged contact with any solution of an alkaline pH as it will result in hydrolysis of the drug. Do not mix ELLENCE with heparin or fluorouracil due to chemical incompatibility that may lead to precipitation.

ELLENCE can be used in combination with other antitumor agents, but do not mix with other drugs in the same syringe.

Administration

Administer ELLENCE into the tubing of a freely flowing intravenous infusion (0.9% sodium chloride or 5% glucose solution). Patients receiving initial therapy at the recommended starting doses of 100–120 mg/m^2 should generally have ELLENCE infused over 15–20 minutes.

For patients who require lower ELLENCE starting doses due to organ dysfunction or who require modification of ELLENCE doses during therapy, the ELLENCE infusion time may be proportionally decreased, but should not be less than 3 minutes. This technique is intended to minimize the risk of thrombosis or perivenous extravasation, which could lead to severe cellulitis, vesication, or tissue necrosis.

A direct push injection is not recommended due to the risk of extravasation, which may occur even in the presence of adequate blood return upon needle aspiration. Venous sclerosis may result from injection into small vessels or repeated injections into the same vein [see Warnings and Precautions (5.3)].

Storage

Use ELLENCE within 24 hours of first penetration of the rubber stopper. Discard any unused solution.

3 DOSAGE FORMS AND STRENGTHS

Injection: 50 mg/25 mL (2 mg/mL), 200 mg/100 mL (2 mg/mL) clear red solution in a single-dose vial.

4 CONTRAINDICATIONS

ELLENCE is contraindicated in patients with:

- Severe myocardial insufficiency [see Warnings and Precautions (5.1)]
- Recent myocardial infarction or severe arrhythmias, or previous treatment with maximum cumulative dose of anthracyclines [see Warnings and Precautions (5.1)]
- Severe persistent drug-induced myelosuppression [see Warnings and Precautions (5.4)]
- Severe hepatic impairment (defined as Child-Pugh Class C or serum bilirubin level greater than 5 mg/dL) [see Warnings and Precautions (5.5)]
- Severe hypersensitivity to ELLENCE, other anthracyclines, or anthracenediones [see Adverse Reactions (6.1)]

5 WARNINGS AND PRECAUTIONS

5.1 Cardiac Toxicity

ELLENCE and other anthracycline drugs can result in either early (or acute) or late (delayed) cardiac toxicity.

The principal manifestations of early cardiac toxicity are sinus tachycardia and/or electrocardiogram (ECG) abnormalities such as non-specific ST-T wave changes. However, tachycardia (including premature ventricular contractions and ventricular tachycardia), bradycardia, as well as atrioventricular and bundle-branch block have been reported. Early cardiac toxicity does not usually predict the subsequent occurrence of delayed cardiotoxicity and generally should not be considered a reason for suspending treatment with ELLENCE.

Delayed cardiac toxicity is manifested by reduced left ventricular ejection fraction (LVEF) and/or signs and symptoms of congestive heart failure (CHF). If it occurs, late cardiotoxicity usually develops late during therapy with ELLENCE or within 2 to 3 months after completion of treatment, but there are reports of it occurring several months to years after treatment termination. In a retrospective survey, including 9144 patients, mostly with solid tumors in advanced stages, the probability of developing CHF increased with increasing cumulative doses of ELLENCE (Figure 1). In another retrospective survey of 469 ELLENCE-treated patients with metastatic or early breast cancer, the reported risk of CHF was comparable to that observed in the larger study of over 9000 patients.

Given the risk of cardiac toxicity, cumulative doses of 900 mg/m^2 ELLENCE should generally be avoided.

Figure 1. Risk of CHF in 9144 Patients Treated with ELLENCE

Prior history of cardiovascular disease, prior or concomitant radiotherapy to the mediastinal/pericardial area, previous therapy with other anthracyclines or anthracenediones, and concomitant use of other cardiotoxic drugs, increase the risk of developing late cardiac toxicity. Avoid administration of ELLENCE in combination with other cardiotoxic drugs. Although not formally tested, it is probable that the toxicity of ELLENCE and other anthracyclines or anthracenediones is additive. Cardiac toxicity with ELLENCE may occur at lower cumulative doses whether or not cardiac risk factors are present. Patients receiving ELLENCE after stopping treatment with other cardiotoxic drugs, especially those with long half-lives such as trastuzumab, may be at increased risk of developing cardiotoxicity [see Dosage and Administration (2) and Drug Interaction (7.1)].

Perform a baseline ECG and evaluation of LVEF prior to initiating treatment with ELLENCE. Monitor LVEF during the course of treatment and consider discontinuation of ELLENCE if LVEF decrease and/or signs or symptoms of CHF develop. Closely monitor patients with other risk factors for cardiac toxicity, particularly prior administration of anthracycline or anthracenedione.

5.2 Secondary Malignancies

The risk of developing secondary acute myelogenous leukemia and myelodysplastic syndrome (MDS), is increased following treatment with ELLENCE and other anthracyclines. Cumulative risk of secondary acute myelogenous leukemia or myelodysplastic syndrome (AML/MDS) of about 0.27% at 3 years, 0.46% at 5 years, and 0.55% at 8 years. These leukemias generally occur within 1 to 3 years of treatment [see Adverse Reactions (6.1)].

5.3 Extravasation and Tissue Necrosis

Extravasation of ELLENCE can result in severe local tissue injury manifesting as blistering, ulceration, and necrosis requiring wide excision of the affected area and skin grafting. Extravasation should be considered if a patient experiences a burning or stinging sensation or shows other evidence indicating peri-venous infiltration or extravasation; however, extravasation may be present in patients who do not experience a stinging or burning sensation or when blood return is present on aspiration of the infusion needle.

Venous sclerosis may result from an injection into a small vessel or from repeated injections into the same vein. Administer ELLENCE slowly into the tubing of a freely running intravenous infusion. Patients receiving initial therapy at the recommended starting doses of 100–120 mg/m^2 should have ELLENCE infused over 15–20 minutes. For patients who require lower ELLENCE starting doses due to organ dysfunction or who require modification of ELLENCE doses during therapy, the ELLENCE infusion time may be proportionally decreased, but should not be less than 3 minutes [see Dosage and Administration (2.3)]. If possible, avoid veins over joints or in extremities with compromised venous or lymphatic drainage. Facial flushing, as well as local erythematous streaking along the vein, may be indicative of excessively rapid administration. It may precede local phlebitis or thrombophlebitis.

Immediately terminate infusion and restart in another vein if a burning or stinging sensation indicates perivenous infiltration. Perivenous infiltration may occur without causing pain. If extravasation is suspected, immediately discontinue the intravenous injection or continuous intravenous infusion [see Dosage and Administration (2.3)]. Apply ice to the site intermittently for 15 minutes, 4 times a day for 3 days. If appropriate, administer dexrazoxane at the site of extravasation as soon as possible and within the first 6 hours after extravasation.

5.4 Severe Myelosuppression

ELLENCE can cause severe myelosuppression [see Adverse Reactions (6.1). Obtain complete blood counts prior to each treatment and carefully monitor patients during treatment for possible clinical complications due to myelosuppression. Delay the next dose of ELLENCE if severe myelosuppression has not improved. Consider dose reduction for patients with prolonged myelosuppression based on the severity of reaction [see Dosage and Administration (2.3)].

5.5 Use in Patients with Hepatic Impairment

The major route of elimination of epirubicin is the hepatobiliary system [see Clinical Pharmacology (12.3)]. Evaluate serum total bilirubin and AST levels before and during treatment with ELLENCE. Patients with elevated bilirubin or AST may experience slower clearance of drug with an increase in overall toxicity. Lower doses are recommended in these patients [see Dosage and Administration (2.2)]. Patients with severe hepatic impairment have not been evaluated; therefore, do not use ELLENCE in this patient population [see Contraindications (4)].

5.6 Use in Patients with Renal Impairment

Assess serum creatinine before and during therapy. Dosage adjustment is necessary in patients with serum creatinine >5 mg/dL [see Dosage and Administration (2.2) and Clinical Pharmacology (12.3)]. Patients undergoing dialysis have not been studied.

5.7 Tumor-Lysis Syndrome

ELLENCE can induce tumor lysis syndrome in patients with rapidly growing tumors. Evaluate blood uric acid levels, potassium, calcium, phosphate, and creatinine after initial treatment. Consider hydration, urine alkalinization, and prophylaxis with allopurinol to minimize hyperuricemia and potential complications of tumor lysis syndrome.

5.8 Immunosuppressant Effects/Increased Susceptibility to Infections

Administration of live or live-attenuated vaccines in patients immunocompromised by chemotherapeutic agents including epirubicin, may result in serious or fatal infections. Avoid vaccination with a live vaccine in patients receiving ELLENCE. Killed or inactivated vaccines may be administered; however, the response to such vaccines may be diminished.

5.9 Thrombophlebitis and Thromboembolic Events

Thrombophlebitis and thromboembolic events, including pulmonary embolism (in some cases fatal) have been reported with the use of ELLENCE.

5.10 Potentiation of Radiation Toxicity and Radiation Recall

ELLENCE can increase radiation-induced toxicity to the myocardium, mucosa, skin, and liver. Radiation recall, including but not limited to cutaneous and pulmonary toxicity, can occur in patients who receive ELLENCE after prior radiation therapy.

5.11 Embryo-Fetal Toxicity

Based on findings from animals and its mechanism of action, ELLENCE can cause fetal harm when administered to a pregnant woman; avoid the use of ELLENCE during the 1st trimester. Available human data do not establish the presence or absence of major birth defects and miscarriage related to the use of epirubicin during the 2nd and 3rd trimesters. In animal reproduction studies, epirubicin was embryo-fetal lethal and caused structural abnormalities in rats and rabbits at doses less than the maximum recommended human dose on a body surface area basis. Advise pregnant women and females of reproductive potential of the potential risk to a fetus. Advise female patients of reproductive potential to use effective contraception during treatment and for 6 months after the last dose of ELLENCE. Advise male patients with female partners of reproductive potential to use effective contraception during treatment and for 3 months after the last dose of ELLENCE. Advise male patients with pregnant partners to use condoms during treatment and for at least 7 days after the last dose of ELLENCE [see Use in Specific Populations (8.1, 8.3), Clinical Pharmacology (12.1), and Nonclinical Toxicology (13.1)].

6 ADVERSE REACTIONS

The following clinically significant adverse reactions are described elsewhere in the labeling:

- Cardiac Toxicity [see Warnings and Precautions (5.1)]
- Secondary Malignancies [see Warnings and Precautions (5.2)]
- Extravasation and Tissue Necrosis [see Warnings and Precautions (5.3)]
- Severe Myelosuppression [see Warnings and Precautions (5.4)]
- Tumor-Lysis Syndrome [see Warnings and Precautions (5.7)]
- Thrombophlebitis and Thromboembolic Events [see Warnings and Precautions (5.9)]
- Potentiation of Radiation Toxicity and Radiation Recall [see Warnings and Precautions (5.10)]

6.1 Clinical Trials Experience

Because clinical trials are conducted under widely varying conditions, adverse reactions rates observed in the clinical trials of a drug cannot be directly compared to rates in the clinical trials of another drug and may not reflect the rates observed in practice.

The safety of ELLENCE was evaluated in two studies (Studies MA-5 and GFEA-05) evaluating combination regimens in patients with early breast cancer [see Clinical Studies (14.1)]. Of the 1260 patients treated in these studies, 620 patients received the higher-dose ELLENCE regimen (FEC-100/CEF-120), 280 patients received the lower-dose ELLENCE regimen (FEC-50), and 360 patients received CMF. Serotonin-specific antiemetic therapy and colony-stimulating factors were not used in these trials. Clinically relevant adverse reactions are summarized in Table 1.

Table 1. Adverse Reactions in Patients with Early Breast Cancer
Event | % of Patients
 | FEC-100/CEF-120 (N=620) |  | FEC-50 (N=280) |  | CMF (N=360)
 | Grades 1–4 | Grades 3/4 | Grades 1–4 | Grades 3/4 | Grades 1–4 | Grades 3/4
Hematologic
Leukopenia | 80 | 59 | 50 | 1.5 | 98 | 60
Neutropenia | 80 | 67 | 54 | 11 | 96 | 78
Anemia | 72 | 6 | 13 | 0 | 71 | 0.9
Thrombocytopenia | 49 | 5 | 4.6 | 0 | 51 | 3.6
Endocrine
Amenorrhea | 72 | 0 | 69 | 0 | 68 | 0
Hot flashes | 39 | 4 | 5 | 0 | 69 | 6
Body as a Whole
Lethargy | 46 | 1.9 | 1.1 | 0 | 73 | 0.3
Fever | 5 | 0 | 1.4 | 0 | 4.5 | 0
Gastrointestinal
Nausea/vomiting | 92 | 25 | 83 | 22 | 85 | 6
Mucositis | 59 | 9 | 9 | 0 | 53 | 1.9
Diarrhea | 25 | 0.8 | 7 | 0 | 51 | 2.8
Anorexia | 2.9 | 0 | 1.8 | 0 | 6 | 0.3
Infection
Infection | 22 | 1.6 | 15 | 0 | 26 | 0.6
Febrile neutropenia | NA | 6 | 0 | 0 | NA | 1.1
Ocular
Conjunctivitis/keratitis | 15 | 0 | 1.1 | 0 | 38 | 0
Skin
Alopecia | 96 | 57 | 70 | 19 | 84 | 7
Local toxicity | 20 | 0.3 | 2.5 | 0.4 | 8 | 0
Rash/itch | 9 | 0.3 | 1.4 | 0 | 14 | 0
Skin changes | 4.7 | 0 | 0.7 | 0 | 7 | 0
FEC & CEF = cyclophosphamide + ELLENCE + fluorouracil; CMF = cyclophosphamide + methotrexate + fluorouracil; NA = not available
Grade 1 or 2 changes in transaminase levels were observed but were more frequently seen with CMF than with CEF.

Delayed Events

Table 2 describes the incidence of delayed adverse reactions in patients participating in the MA-5 and GFEA-05 trials.

Table 2. Long-Term Adverse Reactions in Patients with Early Breast Cancer
Event | % of Patients
Event | FEC-100/CEF-120 (N=620) | FEC-50 (N=280) | CMF (N=360)
Cardiac events
Asymptomatic drops in LVEF | 2.1 [In study MA-5, cardiac function was not monitored after 5 years.] | 1.4 | 0.8
CHF | 1.5 | 0.4 | 0.3
Leukemia
AML | 0.8 | 0 | 0.3
Two cases of acute lymphoid leukemia (ALL) were also observed in patients receiving ELLENCE. However, an association between anthracyclines such as ELLENCE and ALL has not been clearly established.

Hematologic

Dose-dependent, reversible leukopenia and/or neutropenia is the predominant manifestation of hematologic toxicity associated with ELLENCE and represents the most common acute dose-limiting toxicity of this drug. In most cases, the white blood cell (WBC) nadir is reached 10 to 14 days from drug administration. Leukopenia/neutropenia is usually transient, with WBC and neutrophil counts generally returning to normal values by Day 21 after drug administration. As with other cytotoxic agents, ELLENCE at the recommended dose in combination with cyclophosphamide and fluorouracil can produce severe leukopenia and neutropenia. Severe thrombocytopenia and anemia may also occur. Clinical consequences of severe myelosuppression include fever, infection, septicemia, septic shock, hemorrhage, tissue hypoxia, symptomatic anemia, or death. If myelosuppressive complications occur, use appropriate supportive measures (e.g., intravenous antibiotics, colony-stimulating factors, transfusions). Myelosuppression requires careful monitoring. Assess total and differential WBC, red blood cell (RBC), and platelet counts before and during each cycle of therapy with ELLENCE [see Warnings and Precautions (5.4)].

Gastrointestinal

A dose-dependent mucositis (mainly oral stomatitis, less often esophagitis) may occur in patients treated with ELLENCE. Clinical manifestations of mucositis may include a pain or burning sensation, erythema, erosions, ulcerations, bleeding, or infections. Mucositis generally appears early after drug administration and, if severe, may progress over a few days to mucosal ulcerations; most patients recover from this adverse event by the third week of therapy. Hyperpigmentation of the oral mucosa may also occur. Nausea, vomiting, and occasionally diarrhea and abdominal pain can also occur. Severe vomiting and diarrhea may produce dehydration. Antiemetics may reduce nausea and vomiting; consider prophylactic use of antiemetics before therapy [see Dosage and Administration (2.1)].

Cutaneous and Hypersensitivity Reactions

Alopecia occurs frequently, but is usually reversible, with hair regrowth occurring within 2 to 3 months from the termination of therapy. Flushes, skin and nail hyperpigmentation, photosensitivity, and hypersensitivity to irradiated skin (radiation-recall reaction) have been observed. Urticaria and anaphylaxis have been reported in patients treated with ELLENCE; signs and symptoms of these reactions may vary from skin rash and pruritus to fever, chills, and shock.

Cardiovascular

Serious drug-related cardiovascular adverse events that occurred during clinical trials with ELLENCE, administered in different indications, include ventricular tachycardia, AV block, bundle branch block, bradycardia and thromboembolism.

Secondary Leukemia

An analysis of 7110 patients who received adjuvant treatment with ELLENCE in controlled clinical trials as a component of poly-chemotherapy regimens for early breast cancer, showed a cumulative risk of secondary acute myelogenous leukemia or myelodysplastic syndrome (AML/MDS) of about 0.27% (approximate 95% CI, 0.14–0.40) at 3 years, 0.46% (approximate 95% CI, 0.28–0.65) at 5 years, and 0.55% (approximate 95% CI, 0.33–0.78) at 8 years. The risk of developing AML/MDS increased with increasing ELLENCE cumulative doses as shown in Figure 2.

Figure 2. Risk of AML/MDS in 7110 Patients Treated with ELLENCE

The cumulative probability of developing AML/MDS was found to be particularly increased in patients who received more than the maximum recommended cumulative dose of ELLENCE (720 mg/m^2) or cyclophosphamide (6,300 mg/m^2), as shown in Table 3.

Table 3. Cumulative Probability of AML/MDS in Relation to Cumulative Doses of ELLENCE and Cyclophosphamide
Years from Treatment Start | Cumulative Probability of Developing AML/MDS % (95% CI)
Years from Treatment Start | Cyclophosphamide Cumulative Dose ≤6,300 mg/m^2 |  | Cyclophosphamide Cumulative Dose >6,300 mg/m^2
Years from Treatment Start | ELLENCE Cumulative Dose ≤720 mg/m^2 N=4760 | ELLENCE Cumulative Dose >720 mg/m^2 N=111 | ELLENCE Cumulative Dose ≤720 mg/m^2 N=890 | ELLENCE Cumulative Dose >720 mg/m^2 N=261
3 | 0.12 (0.01–0.22) | 0.00 (0.00–0.00) | 0.12 (0.00–0.37) | 4.37 (1.69–7.05)
5 | 0.25 (0.08–0.42) | 2.38 (0.00–6.99) | 0.31 (0.00–0.75) | 4.97 (2.06–7.87)
8 | 0.37 (0.13–0.61) | 2.38 (0.00–6.99) | 0.31 (0.00–0.75) | 4.97 (2.06–7.87)

6.2 Postmarketing Experience

The following adverse reactions have been identified during post-approval use of ELLENCE. Because these reactions are reported voluntarily from a population of uncertain size, it is not always possible to reliably estimate their frequency or establish a causal relationship to drug exposure.

Infections and infestations: sepsis, pneumonia

Immune system disorders: anaphylaxis

Metabolism and nutrition disorders: dehydration, hyperuricemia

Vascular disorders: shock, hemorrhage, embolism arterial, thrombophlebitis, phlebitis

Respiratory, thoracic and mediastinal disorders: pulmonary embolism

Gastrointestinal disorders: erosions, ulcerations, pain or burning sensation, bleeding, hyperpigmentation of the oral mucosa

Skin and subcutaneous tissue disorders: erythema, flushes, skin and nail hyperpigmentation, photosensitivity, hypersensitivity to irradiated skin (radiation-recall reaction), urticaria

Renal and urinary disorders: red coloration of urine for 1 to 2 days after administration

General disorders and administration site conditions: fever, chills

Injury, poisoning and procedural complications: chemical cystitis (following intravesical administration)

7 DRUG INTERACTIONS

7.1 Cardiotoxic Agents

Closely monitor cardiac function when ELLENCE is used in combination with other cardiotoxic agents. Patients receiving ELLENCE after stopping treatment with other cardiotoxic agents, especially those with long half-lives such as trastuzumab, may be at an increased risk of developing cardiotoxicity [see Dosage and Administration (2) and Warnings and Precautions (5.1)]. Trastuzumab may persist in the circulation for up to 7 months. Therefore, avoid anthracycline-based therapy for up to 7 months after stopping trastuzumab when possible. Monitor the patient's cardiac function closely if anthracyclines are used before this time.

Concomitant use of ELLENCE with other cardioactive compounds that could cause heart failure (e.g., calcium channel blockers), requires close monitoring of cardiac function throughout treatment.

7.2 Cimetidine

Cimetidine increases the exposure to epirubicin [see Clinical Pharmacology (12.3)]. Discontinue cimetidine during treatment with ELLENCE.

7.3 Other Cytotoxic Drugs

ELLENCE used in combination with other cytotoxic drugs may show on-treatment additive toxicity, especially hematologic and gastrointestinal effects.

Paclitaxel:

The administration of epirubicin immediately prior to or after paclitaxel increased the systemic exposure of epirubicin, epirubicinol and 7-deoxydoxorubicin aglycone [see Clinical Pharmacology (12.3)].

Docetaxel:

The administration of epirubicin immediately prior to or after docetaxel did not have an effect on the systemic exposure of epirubicin, but increased the systemic exposure of epirubicinol and 7-deoxydoxorubicin aglycone [see Clinical Pharmacology (12.3)].

7.4 Radiation Therapy

There are few data regarding the coadministration of radiation therapy and ELLENCE. In adjuvant trials of ELLENCE-containing CEF-120 or FEC-100 chemotherapies, breast irradiation was delayed until after chemotherapy was completed. This practice resulted in no apparent increase in local breast cancer recurrence relative to published accounts in the literature. A small number of patients received ELLENCE-based chemotherapy concomitantly with radiation therapy but had chemotherapy interrupted in order to avoid potential overlapping toxicities. It is likely that use of ELLENCE with radiotherapy may sensitize tissues to the cytotoxic actions of irradiation. Administration of ELLENCE after previous radiation therapy may induce an inflammatory recall reaction at the site of the irradiation.

8 USE IN SPECIFIC POPULATIONS

8.1 Pregnancy

Risk Summary

Based on findings from animal studies and its mechanism of action, ELLENCE can cause fetal harm when administered to a pregnant woman [see Clinical Pharmacology (12.1)]; avoid the use of ELLENCE during the 1st trimester. Available human data do not establish the presence or absence of major birth defects and miscarriage related to the use of epirubicin during the 2nd and 3rd trimesters. There are reports of fetal and/or neonatal cardiotoxicity following in utero exposure to epirubicin (see Clinical Considerations). In animal reproduction studies in pregnant rats, epirubicin was embryo-fetal lethal and caused structural abnormalities when administered during organogenesis at doses less than the maximum recommended human dose on a body surface area basis (see Data). Advise pregnant women and females of reproductive potential of the potential risk to a fetus.

The estimated background risk of major birth defects and miscarriage for the indicated population is unknown. In the U.S. general population, the estimated background risk of major birth defects and miscarriage in clinically recognized pregnancies is 2 to 4% and 15 to 20%, respectively.

Clinical Considerations

Fetal/Neonatal Adverse Reactions

There have been rare reports of fetal and/or neonatal transient ventricular hypokinesia, transient elevation of cardiac enzymes, and a case of fetal demise from suspected anthracycline-induced cardiotoxicity following in utero exposure to epirubicin in 2nd and/or 3rd trimesters. Cardiotoxicity is a known risk of anthracycline treatment in adults [see Warnings and Precautions (5.1)]. Monitor the fetus and/or neonate for cardiotoxicity and perform testing consistent with community standards of care.

Data

Animal Data

Intravenous administration of 0.8 mg/kg/day epirubicin (about 0.04 times the maximum recommended single human dose on a body surface area basis) to rats during Days 5 to 15 of gestation resulted in embryofetal lethality (increased resorptions and post-implantation loss) and caused fetal growth retardation (decreased body weight). Intravenous administration of 2 mg/kg/day epirubicin (about 0.1 times the maximum recommended single human dose on a body surface area basis) to rats on Days 9 and 10 of gestation resulted in embryo-fetal lethality (increased late resorptions, post-implantation losses, and dead fetuses; and decreased live fetuses), retarded fetal growth (decreased body weight), and caused decreased placental weight and numerous external (anal atresia, misshapen tail, abnormal genital tubercle), visceral (primarily gastrointestinal, urinary, and cardiovascular systems), and skeletal (deformed long bones and girdles, rib abnormalities, irregular spinal ossification) malformations. Administration of intravenous epirubicin to rabbits at doses up to 0.2 mg/kg/day (about 0.02 times the maximum recommended single human dose on a body surface area basis) during Days 6 to 18 of gestation was not teratogenic, but a maternally toxic dose of 0.32 mg/kg/day increased abortions and delayed ossification. Administration of a maternally toxic intravenous dose of 1 mg/kg/day epirubicin to rabbits (about 0.1 times the maximum recommended single human dose on a body surface area basis) on Days 10 to 12 of gestation induced abortion, but no other signs of teratogenicity were observed. When doses up to 0.5 mg/kg/day epirubicin were administered to rat dams from Day 17 of gestation to Day 21 after delivery (about 0.025 times the maximum recommended single human dose on a body surface area basis), no permanent changes were observed in the development, functional activity, behavior, or reproductive performance of the offspring.

8.2 Lactation

Risk Summary

There are no data on the presence of epirubicin in human milk, the effects on the breastfed child, or the effects on milk production. Epirubicin is present in rat milk (see Data). When a drug is present in animal milk it is likely the drug will be present in human milk. Because of the potential for serious adverse reactions in the breastfed child, advise lactating women not to breastfeed during treatment with ELLENCE and for at least 7 days after the last dose.

Data

Animal Data

In a peri- and post-natal study, epirubicin was present in milk of rats treated with 0.5 mg/kg/day epirubicin (about 0.025 times the maximum recommended human dose on a body surface area basis).

8.3 Females and Males of Reproductive Potential

Pregnancy Testing

Verify the pregnancy status in female patients of reproductive potential prior to initiating ELLENCE.

Contraception

Females

ELLENCE can cause fetal harm when administered to a pregnant woman [see Use in Specific Populations (8.1)]. Advise female patients of reproductive potential to use effective contraception during treatment and for 6 months after the last dose of ELLENCE.

Males

Based on its mechanism of action and genotoxicity studies, advise male patients with female partners of reproductive potential to use effective contraception during treatment and for 3 months after the last dose of ELLENCE. Advise male patients with pregnant partners use condoms during treatment and for at least 7 days after the last dose of ELLENCE [see Clinical Pharmacology (12.1) and Nonclinical Toxicology (13.1)].

Infertility

Females

Based on clinical findings and animal studies, ELLENCE may impair female fertility and result in amenorrhea. Premature menopause can occur. Recovery of menses and ovulation is related to age at treatment [see Nonclinical Toxicology (13.1)].

Males

Based on clinical findings and animal studies, ELLENCE may cause oligospermia, azoospermia, and permanent loss of fertility. Sperm counts have been reported to return to normal levels in some men. This may occur several years after the end of therapy [see Nonclinical Toxicology (13.1)].

8.4 Pediatric Use

Safety and effectiveness of ELLENCE have not been established in pediatric patients. Pediatric patients may be at greater risk for anthracycline-induced acute manifestations of cardiotoxicity or late cardiovascular dysfunction. The pharmacokinetics of epirubicin in pediatric patients have not been evaluated.

8.5 Geriatric Use

Clinical experience in patients who were 65 years of age and older who received ELLENCE chemotherapy regimens for primary breast cancer showed no overall differences in safety and effectiveness compared with younger patients.

In elderly female patients, closely monitor for increased toxicity due to the risk of decreased clearance of epirubicin [see Clinical Pharmacology (12.3)].

8.6 Hepatic Impairment

Epirubicin is eliminated by both hepatic metabolism and biliary excretion and clearance is reduced in patients with hepatic dysfunction. Do not treat patients with severe hepatic impairment with ELLENCE [see Contraindications (4)]. Reduce the starting dose for patients with less severe hepatic impairment [see Dosage and Administration (2.2) and Clinical Pharmacology (12.3)].

8.7 Renal Impairment

No significant alterations in the pharmacokinetics of epirubicin or its major metabolite, epirubicinol, have been observed in patients with serum creatinine <5 mg/dL. Consider lower doses in patients with severe renal impairment (serum creatinine >5 mg/dL), as a reduction in plasma clearance was reported in these patients [see Dosage and Administration (2.3) and Clinical Pharmacology (12.3)]. Patients on dialysis have not been studied.

10 OVERDOSAGE

There is no known antidote for overdoses of ELLENCE. A 36-year-old man with non-Hodgkin's lymphoma received a daily 95 mg/m^2 dose of ELLENCE for 5 consecutive days. Five days later, he developed bone marrow aplasia, grade 4 mucositis, and gastrointestinal bleeding. No signs of acute cardiac toxicity were observed. He was treated with antibiotics, colony-stimulating factors, and antifungal agents, and recovered completely. A 63-year-old woman with breast cancer and liver metastasis received a single 320 mg/m^2 dose of ELLENCE. She was hospitalized with hyperthermia and developed multiple organ failure (respiratory and renal), with lactic acidosis, increased lactate dehydrogenase, and anuria. Death occurred within 24 hours after administration of ELLENCE. Additional instances of administration of doses higher than recommended have been reported at doses ranging from 150 to 250 mg/m^2. The observed adverse events in these patients were qualitatively similar to known toxicities of epirubicin. Most of the patients recovered with appropriate supportive care.

If an overdose occurs, provide supportive treatment (including antibiotic therapy, blood and platelet transfusions, colony-stimulating factors, and intensive care as needed) until the recovery of toxicities. Delayed CHF has been observed months after anthracycline administration. Observe patients carefully over time for signs of CHF and provided with appropriate supportive therapy.

11 DESCRIPTION

ELLENCE (epirubicin hydrochloride injection) is an anthracycline topoisomerase inhibitor for intravenous administration. ELLENCE is supplied as a sterile, clear, red solution and is available in polypropylene vials containing 50 and 200 mg of epirubicin hydrochloride as a preservative-free, ready-to-use solution. Each milliliter of solution contains 2 mg of epirubicin hydrochloride. Inactive ingredients include 9 mg sodium chloride, USP, and water for injection, USP. The pH of the solution has been adjusted to 3.0 with hydrochloric acid and/or sodium hydroxide, NF.

Epirubicin hydrochloride is the 4-epimer of doxorubicin and is a semi-synthetic derivative of daunorubicin. The chemical name is (8S-cis)-10-[(3-amino-2,3,6-trideoxy-α-L- arabino-hexopyranosyl)oxy]-7,8,9,10-tetrahydro6,8,11-trihydroxy-8-(hydroxyacetyl)-1-methoxy-5,12-naphthacenedione hydrochloride. The active ingredient is a red-orange hygroscopic powder, with the empirical formula C27 H29 NO11 HCl and a molecular weight of 579.95. The structural formula is as follows:

12 CLINICAL PHARMACOLOGY

12.1 Mechanism of Action

Epirubicin is an anthracycline cytotoxic agent. Although it is known that anthracyclines can interfere with a number of biochemical and biological functions within eukaryotic cells, the precise mechanisms of epirubicin's cytotoxic and/or antiproliferative properties have not been completely elucidated.

Epirubicin forms a complex with DNA by intercalation of its planar rings between nucleotide base pairs, with consequent inhibition of nucleic acid (DNA and RNA) and protein synthesis.

Such intercalation triggers DNA cleavage by topoisomerase II, resulting in cytocidal activity. Epirubicin also inhibits DNA helicase activity, preventing the enzymatic separation of double-stranded DNA and interfering with replication and transcription. Epirubicin is also involved in oxidation/reduction reactions by generating cytotoxic free radicals. The antiproliferative and cytotoxic activity of epirubicin is thought to result from these or other possible mechanisms.

Epirubicin is cytotoxic in vitro to a variety of established murine and human cell lines and primary cultures of human tumors. It is also active in vivo against a variety of murine tumors and human xenografts in athymic mice, including breast tumors.

12.3 Pharmacokinetics

Epirubicin pharmacokinetics are linear over the dose range of 60 to 150 mg/m^2 and plasma clearance is not affected by the duration of infusion or administration schedule. Pharmacokinetic parameters for epirubicin following 6- to 10-minute, single-dose intravenous infusions of ELLENCE at doses of 60 to 150 mg/m^2 in patients with solid tumors are shown in Table 4. The plasma concentration declined in a triphasic manner with mean half-lives for the alpha, beta, and gamma phases of about 3 minutes, 2.5 hours, and 33 hours, respectively.

Table 4. Summary of Mean (±SD) Pharmacokinetic Parameters in Patients [Advanced solid tumor cancers, primarily of the lung] with Solid Tumors Receiving Intravenous ELLENCE 60 to 150 mg/m^2
Dose [N=6 patients per dose level] (mg/m^2) | Cmax [Plasma concentration at the end of 6 to 10 minutes infusion] (µg/mL) | AUC [Area under the plasma concentration curve] (µg∙h/mL) | t1/2 [Half-life of terminal phase] (hours) | CL [Plasma clearance] (L/hour) | Vss [Steady state volume of distribution] (L/kg)
60 | 5.7 ± 1.6 | 1.6 ± 0.2 | 35.3 ± 9 | 65 ± 8 | 21 ± 2
75 | 5.3 ± 1.5 | 1.7 ± 0.3 | 32.1 ± 5 | 83 ± 14 | 27 ± 11
120 | 9.0 ± 3.5 | 3.4 ± 0.7 | 33.7 ± 4 | 65 ± 13 | 23 ± 7
150 | 9.3 ± 2.9 | 4.2 ± 0.8 | 31.1 ± 6 | 69 ± 13 | 21 ± 7

Distribution

Following intravenous administration, epirubicin is rapidly and widely distributed into the tissues. Binding of epirubicin to plasma proteins, predominantly albumin, is about 77% and is not affected by drug concentration. Epirubicin also appears to concentrate in red blood cells; whole blood concentrations are approximately twice those of plasma.

Metabolism

Epirubicin is extensively and rapidly metabolized by the liver and is also metabolized by other organs and cells, including red blood cells. Four main metabolic routes have been identified:

(1) reduction of the C-13 keto-group with the formation of the 13(S)-dihydro derivative, epirubicinol; (2) conjugation of both the unchanged drug and epirubicinol with glucuronic acid; (3) loss of the amino sugar moiety through a hydrolytic process with the formation of the doxorubicin and doxorubicinol aglycones; and (4) loss of the amino sugar moiety through a redox process with the formation of the 7-deoxy-doxorubicin aglycone and 7-deoxy-doxorubicinol aglycone. Epirubicinol has in vitro cytotoxic activity one-tenth that of epirubicin. As plasma levels of epirubicinol are lower than those of the unchanged drug, they are unlikely to reach in vivo concentrations sufficient for cytotoxicity. No significant activity or toxicity has been reported for the other metabolites.

Excretion

Epirubicin and its major metabolites are eliminated through biliary excretion and, to a lesser extent, by urinary excretion. Mass-balance data from 1 patient found about 60% of the total radioactive dose in feces (34%) and urine (27%). These data are consistent with those from 3 patients with extrahepatic obstruction and percutaneous drainage, in whom approximately 35% and 20% of the administered dose were recovered as epirubicin or its major metabolites in bile and urine, respectively, in the 4 days after treatment.

Effect of Age

A population analysis of plasma data from 36 cancer patients (13 males and 23 females, 20 to 73 years) showed that age affects plasma clearance of epirubicin in female patients. The predicted plasma clearance for a female patient of 70 years of age was about 35% lower than that for a female patient of 25 years of age. An insufficient number of males > 50 years of age were included in the study to draw conclusions about age-related alterations in clearance in males. Although a lower ELLENCE starting dose does not appear necessary in elderly female patients, and was not used in clinical trials, particular care should be taken in monitoring toxicity when ELLENCE is administered to female patients > 70 years of age.

Effect of Gender

In patients ≤ 50 years of age, mean clearance values in adult male and female patients were similar. The clearance of epirubicin is decreased in elderly women.

Effect of Race

The influence of race on the pharmacokinetics of epirubicin has not been evaluated.

Effect of Hepatic Impairment

Epirubicin is eliminated by both hepatic metabolism and biliary excretion and clearance is reduced in patients with hepatic dysfunction. In a study of the effect of hepatic dysfunction, patients with solid tumors were classified into 3 groups. Patients in Group 1 (n=22) had serum AST (SGOT) levels above the upper limit of normal (median: 93 IU/L) and normal serum bilirubin levels (median: 0.5 mg/dL) and were given ELLENCE doses of 12.5 to 90 mg/m^2. Patients in Group 2 had alterations in both serum AST (median: 175 IU/L) and bilirubin levels (median: 2.7 mg/dL) and were treated with an ELLENCE dose of 25 mg/m^2 (n=8). Their pharmacokinetics were compared to those of patients with normal serum AST and bilirubin values, who received ELLENCE doses of 12.5 to 120 mg/m^2. The median plasma clearance of epirubicin was decreased compared to patients with normal hepatic function by about 30% in patients in Group 1 and by 50% in patients in Group 2. Patients with more severe hepatic impairment have not been evaluated [see Dosage and Administration (2.3), and Warnings and Precautions (5.5)].

Effect of Renal Impairment

No significant alterations in the pharmacokinetics of epirubicin or its major metabolite, epirubicinol, have been observed in patients with serum creatinine < 5 mg/dL. A 50% reduction in plasma clearance was reported in four patients with serum creatinine ≥ 5 mg/dL [see Warnings and Precautions (5.6) and Dosing and Administration (2.2)]. Patients on dialysis have not been studied.

Effect of Paclitaxel

The administration of paclitaxel (175–225 mg/m^2 as a 3-hour infusion) immediately before or after epirubicin (90 mg/m^2 as bolus) caused variable increases in the systemic exposure (mean AUC) of epirubicin ranging from 5% to 109%. At same doses of epirubicin and paclitaxel, the mean AUC of the inactive metabolites of epirubicin (epirubicinol and 7-deoxy-aglycone) increased by 120% and 70%, respectively, when paclitaxel was immediately administered after epirubicin. Epirubicin had no effect on the exposure of paclitaxel whether it was administered before or after paclitaxel.

Effect of Docetaxel

The administration of docetaxel (70 mg/m^2 as 1-hour infusion) immediately before or after epirubicin (90 mg/m^2 as bolus) had no effect on the systemic exposure (mean AUC) of epirubicin. However, the mean AUC of epirubicinol and 7-deoxy-aglycone increased by 22.5% and 95%, respectively, when docetaxel was immediately administered after epirubicin compared to epirubicin alone. Epirubicin had no effect on the exposure of docetaxel whether it was administered before or after docetaxel.

Effect of Cimetidine

Coadministration of cimetidine (400 mg twice daily for 7 days starting 5 days before chemotherapy) increased the mean AUC of epirubicin (100 mg/m^2) by 50% and decreased its plasma clearance by 30%.

Drugs metabolized by cytochrome P-450 enzymes

No systematic in vitro or in vivo evaluation has been performed to examine the potential for inhibition or induction by epirubicin of oxidative cytochrome P-450 isoenzymes.

13 NONCLINICAL TOXICOLOGY

13.1 Carcinogenesis, Mutagenesis, Impairment of Fertility

Conventional long-term animal studies to evaluate the carcinogenic potential of epirubicin have not been conducted, but intravenous administration of a single 3.6 mg/kg epirubicin dose to female rats (about 0.2 times the maximum recommended human dose on a body surface area basis) approximately doubled the incidence of mammary tumors (primarily fibroadenomas) observed at 1 year. Administration of 0.5 mg/kg epirubicin intravenously to rats (about 0.025 times the maximum recommended human dose on a body surface area basis) every 3 weeks for ten doses increased the incidence of subcutaneous fibromas in males over an 18-month observation period. In addition, subcutaneous administration of 0.75 or 1.0 mg/kg/day (about 0.015 times the maximum recommended human dose on a body surface area basis) to newborn rats for 4 days on both the first and tenth day after birth for a total of eight doses increased the incidence of animals with tumors compared to controls during a 24-month observation period.

Epirubicin was mutagenic in vitro to bacteria (Ames test) either in the presence or absence of metabolic activation and to mammalian cells (HGPRT assay in V79 Chinese hamster lung fibroblasts) in the absence but not in the presence of metabolic activation. Epirubicin was clastogenic in vitro (chromosome aberrations in human lymphocytes) both in the presence and absence of metabolic activation and was also clastogenic in vivo (chromosome aberration in mouse bone marrow).

In fertility studies in rats, males were given epirubicin daily for 9 weeks and mated with females that were given epirubicin daily for 2 weeks prior to mating and through Day 7 of gestation. When 0.3 mg/kg/day (about 0.015 times the maximum recommended human single dose on a body surface area basis) was administered to both sexes, no pregnancies resulted. No effects on mating behavior or fertility were observed at 0.1 mg/kg/day, but male rats had atrophy of the testes and epididymis, and reduced spermatogenesis. The 0.1 mg/kg/day dose also caused embryolethality. An increased incidence of fetal growth retardation was observed in these studies at 0.03 mg/kg/day (about 0.0015 times the maximum recommended human single dose on a body surface area basis). Multiple daily doses of epirubicin to rabbits and dogs also caused atrophy of male reproductive organs. Single 20.5 and 12 mg/kg doses of intravenous epirubicin caused testicular atrophy in mice and rats, respectively (both approximately 0.5 times the maximum recommended human dose on a body surface area basis). A single dose of 16.7 mg/kg epirubicin caused uterine atrophy in rats.

14 CLINICAL STUDIES

14.1 Adjuvant Treatment of Breast Cancer

Two randomized, open-label, multicenter studies evaluated the use of ELLENCE 100 to 120 mg/m^2 in combination with cyclophosphamide and fluorouracil for the adjuvant treatment of patients with axillary-node positive breast cancer and no evidence of distant metastatic disease (Stage II or III). Study MA-5 evaluated 120 mg/m^2 of ELLENCE per course in combination with cyclophosphamide and fluorouracil (CEF-120 regimen). This study randomized premenopausal and perimenopausal women with one or more positive lymph nodes to an ELLENCE-containing CEF-120 regimen or to a CMF regimen. Study GFEA-05 evaluated the use of 100 mg/m^2 of ELLENCE per course in combination with fluorouracil and cyclophosphamide (FEC-100). This study randomized pre- and postmenopausal women to the FEC-100 regimen or to a lower-dose FEC-50 regimen. In the GFEA-05 study, eligible patients were either required to have ≥ 4 nodes involved with tumor or, if only 1 to 3 nodes were positive, to have negative estrogen- and progesterone-receptors and a histologic tumor grade of 2 or 3. A total of 1281 women participated in these studies. Patients with T4 tumors were not eligible for either study. Table 5 shows the treatment regimens that the patients received. Relapse-free survival was defined as time to occurrence of a local, regional, or distant recurrence, or disease-related death. Patients with contralateral breast cancer, second primary malignancy, or death from causes other than breast cancer were censored at the time of the last visit prior to these events.

Table 5. Treatment Regimens Used in Phase 3 Studies of Patients with Early Breast Cancer
 | Treatment Groups | Agent | Regimen
MA-5 [In women who underwent lumpectomy, breast irradiation was to be administered after completion of study chemotherapy.] N=716 | CEF-120 (total, 6 cycles) [Patients also received prophylactic antibiotic therapy with trimethoprim-sulfamethoxazole or fluoroquinolone for the duration of their chemotherapy.] N=356 CMF (total, 6 cycles) N=360 | Cyclophosphamide ELLENCE Fluorouracil Cyclophosphamide Methotrexate Fluorouracil | 75 mg/m^2 PO, d 1–14, q 28 days 60 mg/m^2 IV, d 1 & 8, q 28 days 500 mg/m^2 IV, d 1 & 8, q 28 days 100 mg/m^2 PO, d 1–14, q 28 days 40 mg/m^2 IV, d 1 & 8, q 28 days 600 mg/m^2 IV, d 1 & 8, q 28 days
GFEA-05 [All women were to receive breast irradiation after the completion of chemotherapy.] N=565 | FEC-100 (total, 6 cycles) N=276 FEC-50 (total, 6 cycles) N=289 Tamoxifen 30 mg daily × 3 years, postmenopausal women, any receptor status | Fluorouracil ELLENCE Cyclophosphamide Fluorouracil ELLENCE Cyclophosphamide | 500 mg/m^2 IV, d 1, q 21 days 100 mg/m^2 IV, d 1, q 21 days 500 mg/m^2 IV, d 1, q 21 days 500 mg/m^2 IV, d 1, q 21 days 50 mg/m^2 IV, d 1, q 21 days 500 mg/m^2 IV, d 1, q 21 days

In the MA-5 trial, the median age of the study population was 45 years. Approximately 60% of patients had 1 to 3 involved nodes and approximately 40% had ≥ 4 nodes involved with tumor. In the GFEA-05 study, the median age was 51 years and approximately half of the patients were postmenopausal. About 17% of the study population had 1 to 3 positive nodes and 80% of patients had ≥ 4 involved lymph nodes. Demographic and tumor characteristics were well-balanced between treatment arms in each study.

Relapse-free survival (RFS) and overall survival (OS) were analyzed using Kaplan-Meier methods in the intent-to-treat (ITT) patient populations in each study. Results were initially analyzed after up to 5 years of follow-up and these results are presented in the text below and in Table 6. Results after up to 10 years of follow-up are presented in Table 6. In Study MA-5, ELLENCE-containing combination therapy (CEF-120) showed significantly longer RFS than CMF (5-year estimates were 62% versus 53%, stratified logrank for the overall RFS p=0.013). The estimated reduction in the risk of relapse was 24% at 5 years. The OS was also greater for the ELLENCE-containing CEF-120 regimen than for the CMF regimen (5-year estimate 77% versus 70%; stratified logrank for overall survival p=0.043; non-stratified logrank p=0.13). The estimated reduction in the risk of death was 29% at 5 years.

In Study GFEA-05, patients treated with the higher-dose ELLENCE regimen (FEC-100) had a significantly longer 5-year RFS (estimated 65% versus 52%, logrank for the overall RFS p=0.007) and OS (estimated 76% versus 65%, logrank for the overall survival p=0.007) than patients given the lower dose regimen (FEC-50). The estimated reduction in risk of relapse was 32% at 5 years. The estimated reduction in the risk of death was 31% at 5 years. Results of follow-up up to 10 years (median follow-up = 8.8 years and 8.3 years, respectively, for Study MA-5 and Study GFEA-05) are presented in Table 6.

Although the trials were not powered for subgroup analyses, in the MA-5 study, improvements in favor of CEF-120 vs. CMF were observed, in RFS and OS both in patients with 1–3 node positive and in those with ≥4 node positive tumor involvement. In the GFEA-05 study, improvements in RFS and OS were observed in both pre-and postmenopausal women treated with FEC-100 compared to FEC-50.

Table 6. Efficacy Results from Phase 3 Studies of Patients with Early Breast Cancer [Based on Kaplan-Meier estimates]
 | MA-5 Study |  | GFEA-05 Study
 | CEF-120 N=356 | CMF N=360 | FEC-100 N=276 | FEC-50 N=289
RFS at 5 yrs (%) | 62 | 53 | 65 | 52
Hazard ratio [Hazard ratio: CMF:CEF-120 in MA-5, FEC-50:FEC-100 in GFEA-05] | 0.76 |  | 0.68
2-sided 95% CI | (0.60, 0.96) |  | (0.52, 0.89)
Logrank Test stratified [Patients in MA-5 were stratified by nodal status (1–3, 4–10, and >10 positive nodes), type of initial surgery (lumpectomy versus mastectomy), and by hormone receptor status (ER or PR positive (≥10 fmol), both negative (<10 fmol), or unknown status). Patients in GFEA-05 were stratified by nodal status (1–3, 4–10, and >10 positive nodes).] | (p = 0.013) |  | (p = 0.007)
OS at 5 yrs (%) | 77 | 70 | 76 | 65
Hazard ratio | 0.71 |  | 0.69
2-sided 95% CI | (0.52, 0.98) |  | (0.51, 0.92)
Logrank Test stratified | (p = 0.043) |  | (p = 0.007)
 | (unstratified p = 0.13)
RFS at 10 yrs (%) | 51 | 44 | 49 | 43
Hazard ratio | 0.78 |  | 0.78
2-sided 95% CI | (0.63, 0.95) |  | (0.62, 0.99)
Logrank Test stratified | (p = 0.017) |  | (p = 0.040)
 | (unstratified p = 0.023) |  | (unstratified p = 0.09)
OS at 10 yrs (%) | 61 | 57 | 56 | 50
Hazard ratio | 0.82 |  | 0.75
2-sided 95% CI | (0.65, 1.04) |  | (0.58, 0.96)
Logrank Test stratified | (p = 0.100) |  | (p = 0.023)
 | (unstratified p = 0.18) |  | (unstratified p = 0.039)

The Kaplan-Meier curves for RFS and OS from Study MA-5 are shown in Figures 3 and 4 and those for Study GFEA-05 are shown in Figures 5 and 6.

Figure 3. Relapse-Free Survival in Study MA-5

Figure 4. Overall Survival in Study MA-5

Figure 5. Relapse-Free Survival in Study GFEA-05

Figure 6. Overall Survival in Study GFEA-05

15 REFERENCES

1. "Hazardous Drugs". OSHA. http://www.osha.gov/SLTC/hazardousdrugs/index.html

16 HOW SUPPLIED/STORAGE AND HANDLING

ELLENCE is available in polypropylene single-dose CYTOSAFE® vials containing 2 mg epirubicin hydrochloride per mL as a sterile, preservative-free, ready-to-use, clear, red solution in the following strengths:

Unit of Sale | Strength
NDC 0009-5091-01; Carton of 1 Single-dose Vial | 50 mg/25 mL; (2 mg/mL)
NDC 0009-5093-01; Carton of 1 Single-dose Vial | 200 mg/100 mL; (2 mg/mL)

Discard unused portion.

ELLENCE is available in ONCO-TAIN® glass vials containing 2 mg epirubicin hydrochloride per mL as a sterile, preservative-free, ready-to-use, clear, red solution in the following strengths:

Unit of Sale | Strength
NDC 0009-5091-25; Carton of 1 Single-dose Vial | 50 mg/25 mL; (2 mg/mL)
NDC 0009-5093-10; Carton of 1 Single-dose Vial | 200 mg/100 mL; (2 mg/mL)

ONCO-TAIN® is the vial external protection system.

Discard unused portion.

STORAGE AND HANDLING

Store refrigerated between 2°C and 8°C (36°F and 46°F). Do not freeze. Protect from light.

Storage of the solution for injection at refrigerated conditions can result in the formation of a gelled product. This gelled product will return to a slightly viscous to mobile solution after 2 to a maximum of 4 hours equilibration at controlled room temperature (15–25°C). Solution for injection should be used within 24 hours after removal from refrigeration.

ELLENCE is a hazardous drug. Follow applicable special handling and disposal procedures^1 [see References (15)].

17 PATIENT COUNSELING INFORMATION

Cardiac Toxicity

Inform patients that there is a risk of irreversible myocardial damage associated with treatment with ELLENCE. Advise patients to immediately contact their healthcare provider or to go to an emergency room for new onset of chest pain, shortness of breath, dizziness, or lightheadedness [see Warnings and Precautions (5.1)].

Secondary Malignancies

Inform patients that there is an increased risk of treatment-related leukemia from ELLENCE [see Warnings and Precautions (5.2)].

Extravasation and Tissue Necrosis

Inform patients that ELLENCE can cause severe injection site reactions. Advise patients to contact a healthcare provider if injection site pain occurs after receiving ELLENCE [see Warnings and Precautions (5.3)].

Severe Myelosuppression

Inform patients that ELLENCE can cause leukopenia, thrombocytopenia, or anemia. Advise patients to contact a healthcare provider for new onset fever or symptoms of infection [see Warnings and Precautions (5.4)].

Nausea and Vomiting

Inform patients that ELLENCE can cause nausea or vomiting. Advise patients to contact a healthcare provider should they develop any severe symptoms [see Adverse Reactions (6.1)].

Common Adverse Reactions

Inform patients of the expected adverse effects of ELLENCE, including diarrhea, stomatitis, and alopecia [see Adverse Reactions (6.1)].

Red Coloration of Urine

Advise patients that their urine may appear red for 1 to 2 days after administration of ELLENCE and that they should not be alarmed [see Adverse Reactions (6.2)].

Embryo-Fetal Toxicity

- Advise pregnant women and females of reproductive potential of the potential risk to a fetus, and to inform their healthcare provider of a known or suspected pregnancy [see Warnings and Precautions (5.11) and Use in Specific Populations (8.1)].
- Advise female patients of reproductive potential to use effective contraception during treatment with ELLENCE and for 6 months after the last dose [see Warnings and Precautions (5.11) and Use in Specific Populations (8.3)].
- Advise male patients with female partners of reproductive potential to use effective contraception during treatment and for 3 months after the last dose of ELLENCE. Advise male patients with pregnant partners to use condoms during treatment and for at least 7 days after the last dose of ELLENCE [see Use in Specific Populations (8.3)].

Lactation

Advise female patients not to breastfeed during treatment with ELLENCE and for at least 7 days after the last dose [see Use in Specific Populations (8.2)].

Infertility

Women treated with ELLENCE may develop irreversible amenorrhea, or premature menopause. Advise patients that ELLENCE may impair female and male fertility [see Use in Specific Populations (8.3)].

This product's labeling may have been updated. For the most recent prescribing information, please visit www.pfizer.com. For medical information about ELLENCE, please visit www.pfizermedinfo.com or call 1-800-438-1985.

LAB-0078-15.0

PRINCIPAL DISPLAY PANEL - 50 mg/25 mL Vial Label

NDC 0009-5091-01
Rx only

Single-dose Vial
Ellence®
(epirubicin hydrochloride
injection)

50 mg/25 mL
(2 mg/mL)

For Intravenous Use Only

PRINCIPAL DISPLAY PANEL - 50 mg/25 mL Vial Carton

NDC 0009-5091-01
Rx only

Single-dose Vial
Ellence®
(epirubicin hydrochloride
injection)

50 mg/25 mL
(2 mg/mL)

For Intravenous Use Only

Pfizer Injectables

PRINCIPAL DISPLAY PANEL - 200 mg/100 mL Vial Label

NDC 0009-5093-01
Rx only

Single-dose Vial
Ellence®
(epirubicin hydrochloride
injection)
200 mg/100 mL
(2 mg/mL)

For Intravenous Use Only

Pfizer Injectables

PRINCIPAL DISPLAY PANEL - 200 mg/100 mL Vial Carton

NDC 0009-5093-01
Rx only

Single-dose Vial
Ellence®
(epirubicin hydrochloride
injection)

200 mg/100 mL
(2 mg/mL)

For Intravenous Use Only

Pfizer Injectables

PRINCIPAL DISPLAY PANEL - 50 mg/25 mL Vial Label ONCO-TAIN®

NDC 0009-5091-25
Rx only

Ellence®
(epirubicin hydrochloride
injection)

50 mg/25 mL
(2 mg/mL)

For Intravenous Use Only
Single-dose Vial.
Discard unused portion.

PRINCIPAL DISPLAY PANEL - 50 mg/25 mL Vial Carton ONCO-TAIN®

NDC 0009-5091-25

One 25 mL Single-dose Vial.
Discard unused portion.

Ellence®
(epirubicin hydrochloride
injection)

50 mg/25 mL
(2 mg/mL)

For Intravenous Use Only

Pfizer
Hospital

Rx only

Warning: Hazardous Drug

PRINCIPAL DISPLAY PANEL - 200 mg/100 mL Vial Label ONCO-TAIN®

NDC 0009-5093-10
Rx only

Ellence®
(epirubicin hydrochloride injection)

200 mg/100 mL
(2 mg/mL)

For Intravenous Use Only
Single-dose Vial.
Discard unused portion.

PRINCIPAL DISPLAY PANEL - 200 mg/100 mL Vial Carton ONCO-TAIN®

NDC 0009-5093-10

One 100 mL Single-dose Vial.
Discard unused portion.

Ellence®
(epirubicin hydrochloride
injection)

200 mg/100 mL
(2 mg/mL)

For Intravenous Use Only

Pfizer
Hospital

Rx only

Warning: Hazardous Drug